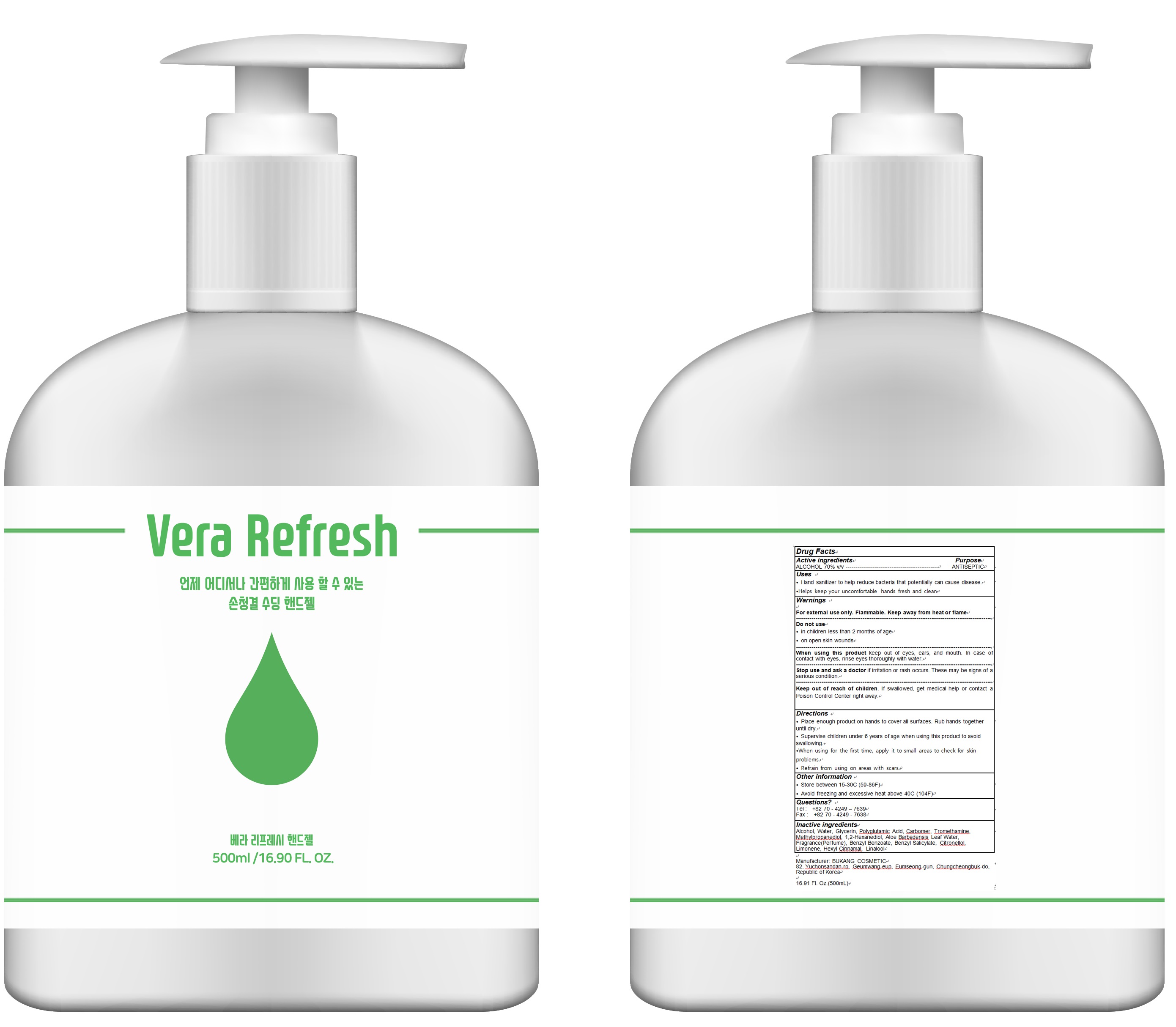 DRUG LABEL: Vera Refresh Hand
NDC: 77445-010 | Form: GEL
Manufacturer: BUKANG COSMETIC
Category: otc | Type: HUMAN OTC DRUG LABEL
Date: 20200518

ACTIVE INGREDIENTS: ALCOHOL 350 mL/500 mL
INACTIVE INGREDIENTS: WATER; Glycerin; CARBOMER HOMOPOLYMER, UNSPECIFIED TYPE; TROLAMINE; Methylpropanediol; 1,2-Hexanediol; ALOE VERA LEAF; Benzyl Benzoate; Benzyl Salicylate; .BETA.-CITRONELLOL, (R)-; LIMONENE, (+)-; .ALPHA.-HEXYLCINNAMALDEHYDE; LINALOOL, (+/-)-

ACTIVE INGREDIENT

Alcohol 70% v/v

INACTIVE INGREDIENT

Water, Glycerin, Polyglutamic Acid, Carbomer, Tromethamine, Methylpropanediol, 1,2-Hexanediol, Aloe Barbadensis Leaf Water, Fragrance(Perfume), Benzyl Benzoate, Benzyl Salicylate, Citronellol, Limonene, Hexyl Cinnamal, Linalool

PURPOSE

Antiseptic

WARNINGS

For external use only. Flammable. Keep away from heat or flame
--------------------------------------------------------------------------------------------------------
Do not use
• in children less than 2 months of age
• on open skin wounds
--------------------------------------------------------------------------------------------------------
When using this product keep out of eyes, ears, and mouth. In case of contact with eyes, rinse eyes thoroughly with water.
--------------------------------------------------------------------------------------------------------
Stop use and ask a doctor if irritation or rash occurs. These may be signs of a serious condition.

KEEP OUT OF REACH OF CHILDREN

If swallowed, get medical help or contact a Poison Control Center right away.

Uses

• Hand sanitizer to help reduce bacteria that potentially can cause disease.
• Helps keep your uncomfortable hands fresh and clean

Directions

• Place enough product on hands to cover all surfaces. Rub hands together until dry.
• Supervise children under 6 years of age when using this product to avoid swallowing.
• When using for the first time, apply it to small areas to check for skin problems.
• Refrain from using on areas with scars.

Other information

• Store between 15-30C (59-86F)
• Avoid freezing and excessive heat above 40C (104F)

Questions?

Tel: +82-70-4249-7639